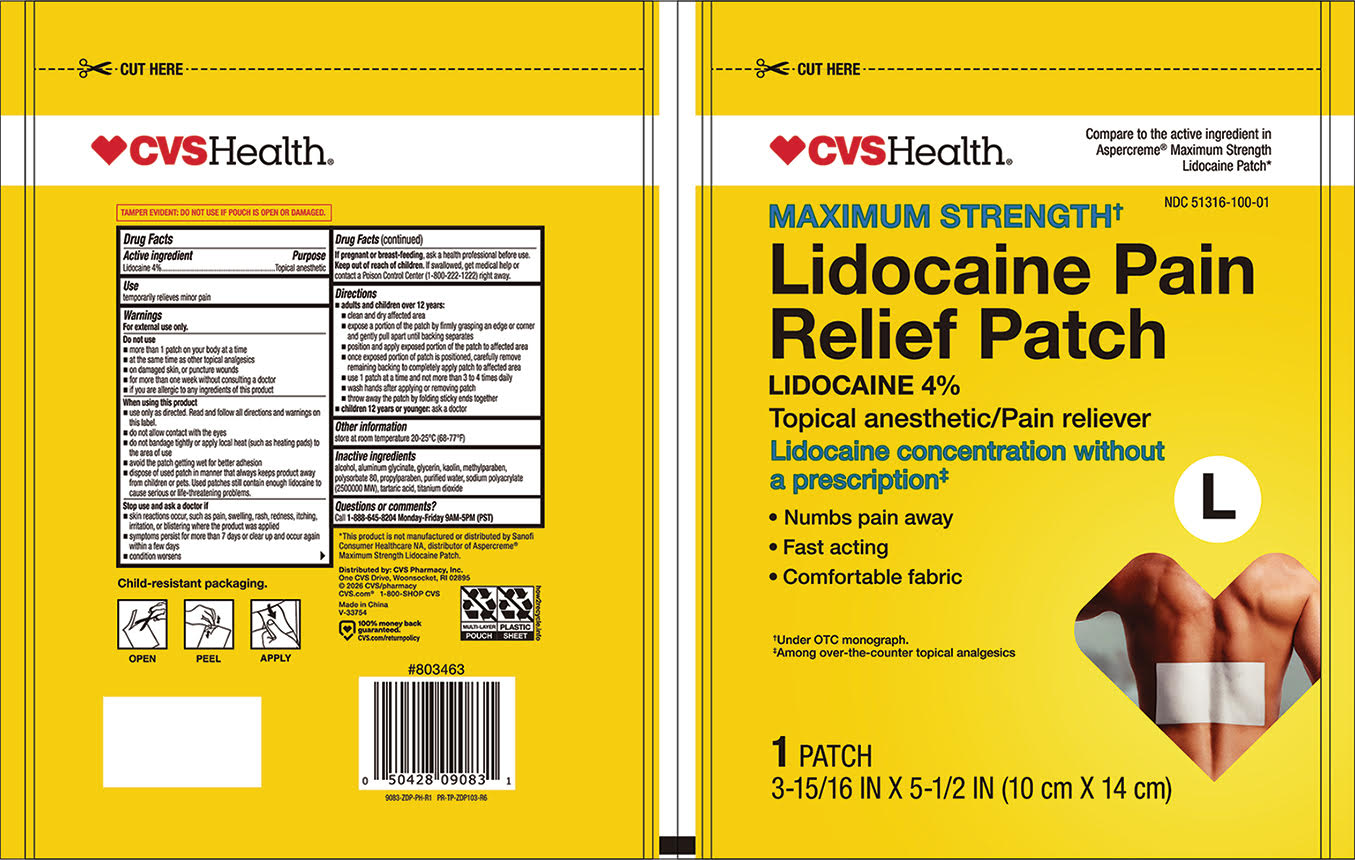 DRUG LABEL: CVS 9083 Maximum Strength Lidocaine 4 Pain Relief Patch 1ct Large
NDC: 51316-100 | Form: PATCH
Manufacturer: CVS PHARMACY, INC
Category: otc | Type: HUMAN OTC DRUG LABEL
Date: 20260123

ACTIVE INGREDIENTS: LIDOCAINE 40 mg/1 g
INACTIVE INGREDIENTS: PROPYLPARABEN; ALCOHOL; TITANIUM DIOXIDE; TARTARIC ACID; ALUMINUM GLYCINATE; KAOLIN; SODIUM POLYACRYLATE (2500000 MW); WATER; METHYLPARABEN; POLYSORBATE 80; GLYCERIN

CVS 9083 Maximum Strength Lidocaine 4% Pain Relief Patch 1ct Large

Active ingredient Purpose
Lidocaine 4%..............................................................Topical anesthetic

Use
temporarily relieves minor pain

Warnings
For external use only.

Do not use
 more than 1 patch on your body at a time
 at the same time as other topical analgesics
 on damaged skin, or puncture wounds
 for more than one week without consulting a doctor
 if you are allergic to any ingredients of this product

When using this product
 use only as directed. Read and follow all directions and warnings on
this label.
 do not allow contact with the eyes
 do not bandage tightly or apply local heat (such as heating pads) to
the area of use
 avoid the patch getting wet for better adhesion
 dispose of used patch in manner that always keeps product away
from children or pets. Used patches still contain enough lidocaine to
cause serious or life-threatening problems.

Stop use and ask a doctor if
 skin reactions occur, such as pain, swelling, rash, redness, itching,
irritation, or blistering where the product was applied
 symptoms persist for more than 7 days or clear up and occur again
within a few days
 condition worsens

PREGNANCY OR BREAST FEEDING

If pregnant or breast-feeding, ask a health professional before use.

Keep out of reach of children. If swallowed, get medical help or
contact a Poison Control Center (1-800-222-1222) right away.

Directions
 adults and children over 12 years:
 clean and dry affected area
 expose a portion of the patch by firmly grasping an edge or corner
and gently pull apart until backing separates
 position and apply exposed portion of the patch to affected area
 once exposed portion of patch is positioned, carefully remove
remaining backing to completely apply patch to affected area
 use 1 patch at a time and not more than 3 to 4 times daily
 wash hands after applying or removing patch
 throw away the patch by folding sticky ends together
 children 12 years or younger: ask a doctor

Other information
store at room temperature 20-25°C (68-77°F)

Inactive ingredients
alcohol, aluminum glycinate, glycerin, kaolin, methylparaben,
polysorbate 80, propylparaben, purified water, sodium polyacrylate
(2500000 MW), tartaric acid, titanium dioxide

Questions or comments?
Call 1-888-645-8204 Monday-Friday 9AM-5PM (PST)

Distributed by: CVS Pharmacy, Inc.

One CVS Drive, Woonsocket, RI 02895

2026 CVS/pharmacy

CVS.com 1-800-SHOP CVS

Made in China